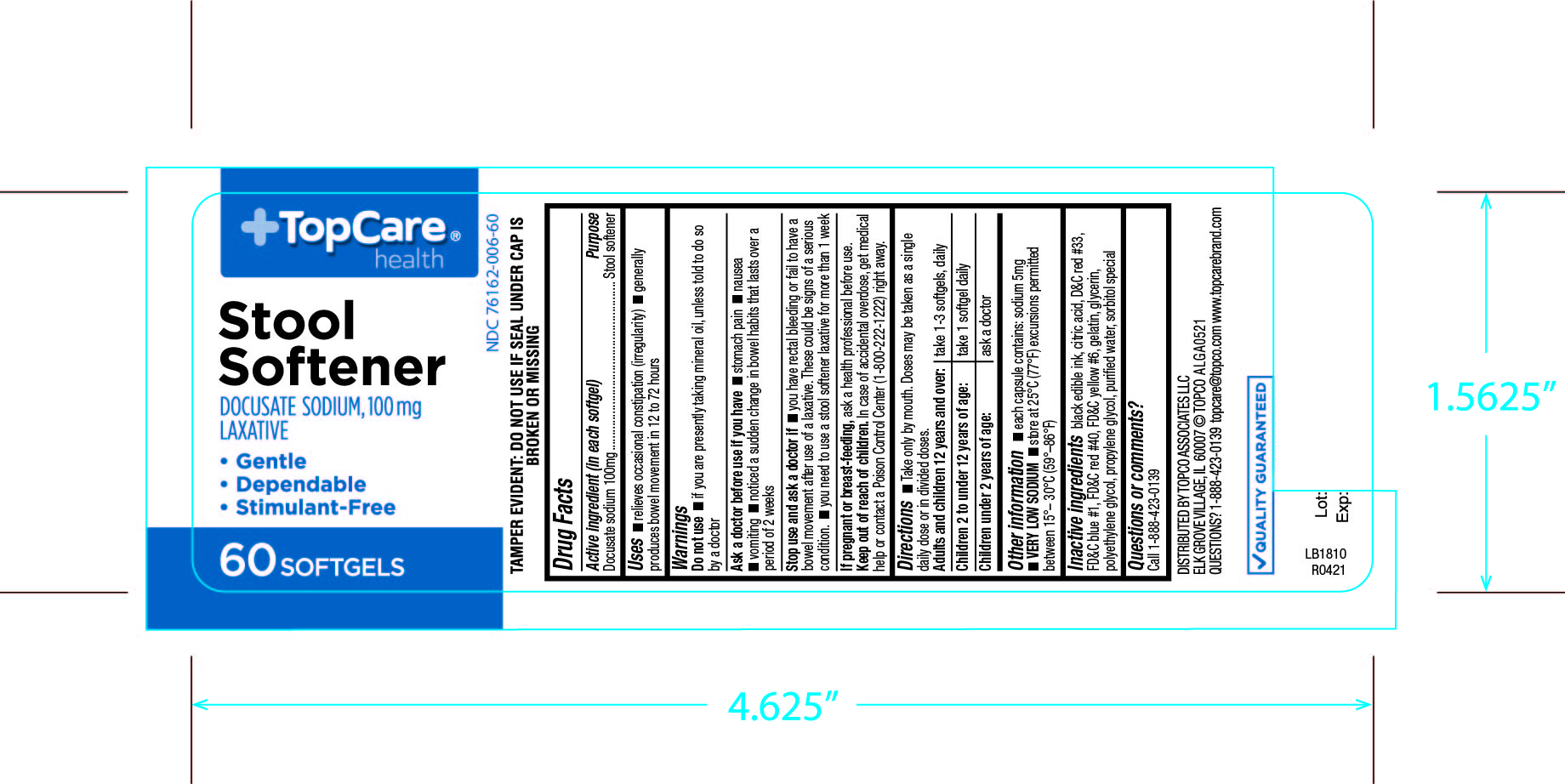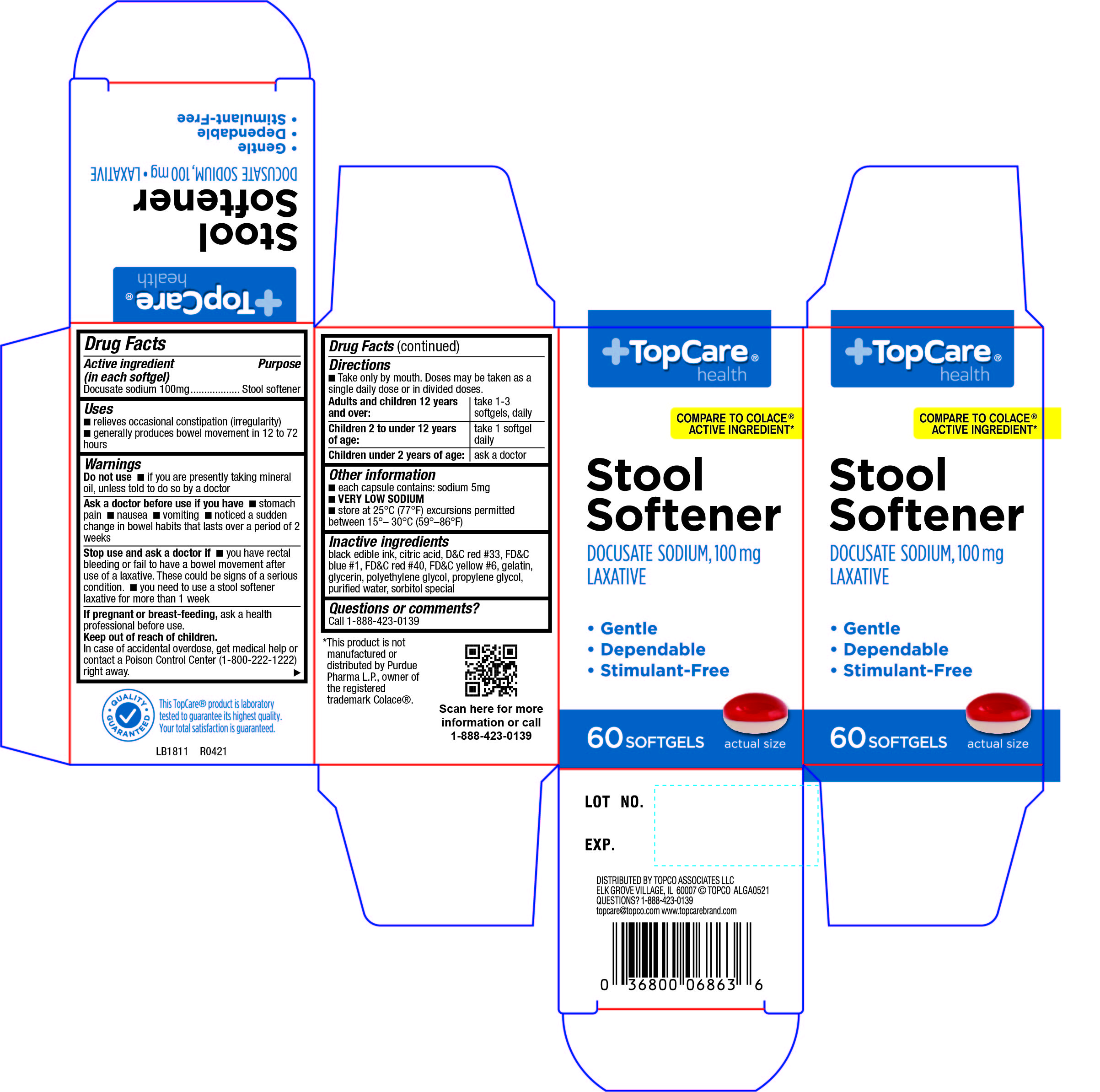 DRUG LABEL: Topcare Stool Softener
NDC: 76162-006 | Form: CAPSULE, LIQUID FILLED
Manufacturer: TopCo Associates, LLC
Category: otc | Type: HUMAN OTC DRUG LABEL
Date: 20210219

ACTIVE INGREDIENTS: DOCUSATE SODIUM 100 mg/1 1
INACTIVE INGREDIENTS: ANHYDROUS CITRIC ACID; D&C RED NO. 33; FD&C BLUE NO. 1; FD&C RED NO. 40; FD&C YELLOW NO. 6; GELATIN; GLYCERIN; POLYETHYLENE GLYCOL 400; PROPYLENE GLYCOL; SORBITOL SOLUTION; WATER

420 Topcare Stool Softener

Active ingredient(s)

Docusate sodium 100mg

Purpose

Stool softener

Use(s)

- relieves occasional constipation (irregularity)
- generally produces bowel movement in 12 to 72 hours

Warnings

Do not use

- if you are presently taking mineral oil, unless told to do so by a doctor

Ask a doctor before use if

you have

- stomach pain
- nausea
- vomiting
- noticed a sudden change in bowel habits that lasts over a period of 2 weeks

Stop use and ask a doctor if

- you have rectal bleeding or fail to have a bowel movement after use of a laxative. These could be signs of a serious condition.
- you need to use a stool softener laxative for more than 1 week

Pregnancy/Breastfeeding

ask a health professional before use.

Keep out of reach of children

In case of accidental overdose, get medical help or contact a Poison Control Center
(1-800-222-1222) right away.

Directions

Take only by mouth. Doses may be taken as a single daily dose or in divided doses.

- Adults and children 12 years and over: Take 1-3 softgels daily
- Children 2 to under 12 years of age : Take 1 softgel daily
  Children under 2 years: Ask a doctor

Other information

- each capsule contains: sodium 5mg
- VERY LOW SODIUM

Storage

- store 25°C (77°F) excursions permitted between 15°– 30°C (59°–86°F)

Inactive ingredients

Black edible ink, citric acid, D&C red #33, FD&C blue #1, FD&C red #40, FD&C yellow #6, gelatin, glycerin, polyethylene glycol, propylene glycol, purified water, sorbitol special

Questions

Call 1-888-952-0050 Monday through Friday 9am-5pm

Principal Display Panel

Stool Softener
Stool Softener